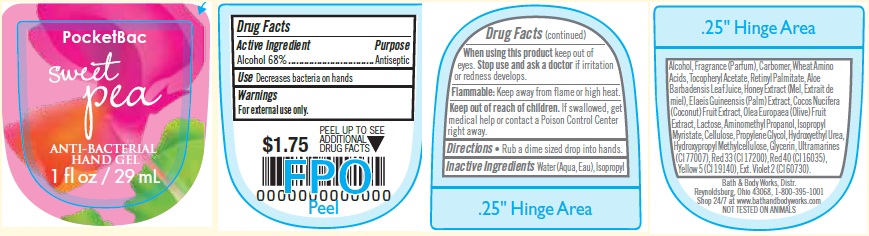 DRUG LABEL: Anti-Bacterial Hand
NDC: 62670-5062 | Form: GEL
Manufacturer: Bath & Body Works, Inc.
Category: otc | Type: HUMAN OTC DRUG LABEL
Date: 20160602

ACTIVE INGREDIENTS: ALCOHOL 68 mL/100 mL
INACTIVE INGREDIENTS: WATER

ACTIVE INGREDIENT

Alcohol 68%

PURPOSE

Antiseptic

USE

Decreases bacteria on hands.

WARNINGS

For external use only.

WHEN USING THIS PRODUCT

keep out of eyes.

STOP USE AND ASK A DOCTOR

if irritation or redness develops.

FLAMMABLE

Keep away from flame or high heat.

KEEP OUT OF REACH OF CHILDREN

If swallowed, get medical help or contact a Poison Control Center right away.

DIRECTIONS

- Rub a dime sized drop into hands.

INACTIVE INGREDIENTS

Water (Aqua, Eau), Isopropyl Alcohol, Fragrance (Parfum), Carbomer, Wheat Amino Acids, Tocopheryl Acetate, Retinyl Palmitate, Aloe
Barbadensis Leaf Juice, Honey Extract (Mel, Extrait de miel), Elaeis Guineensis (Palm) Extract, Cocos Nucifera (Coconut) Fruit Extract, Olea Europaea (Olive) Fruit Extract, Lactose, Aminomethyl Propanol, Isopropyl Myristate, Cellulose, Propylene Glycol, Hydroxyethyl Urea, Hydroxypropyl Methylcellulose, Glycerin, Ultramarines (CI 77007), Red 33 (CI 17200), Red 40 (CI 16035), Yellow 5 (CI 19140), Ext. Violet 2 (CI 60730).

COMPANY INFORMATION

Bath & Body Works, Distr.

Reynoldsburg, Ohio 43068

1-800-395-1001

www.bathandbodyworks.com